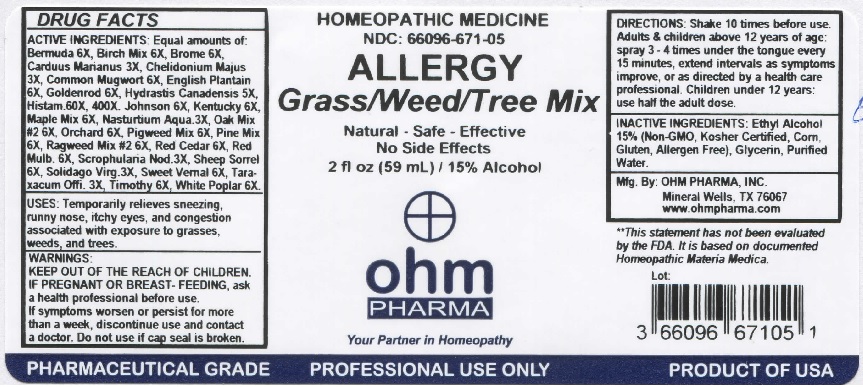 DRUG LABEL: OHM Allergy Grass, Weed, Tree Mix
NDC: 66096-671 | Form: SPRAY
Manufacturer: OHM PHARMA INC.
Category: homeopathic | Type: HUMAN OTC DRUG LABEL
Date: 20210111

ACTIVE INGREDIENTS: CYNODON DACTYLON 6 [hp_X]/59 mL; BETULA PENDULA WHOLE 6 [hp_X]/59 mL; BROMUS SECALINUS TOP 6 [hp_X]/59 mL; MILK THISTLE 3 [hp_X]/59 mL; CHELIDONIUM MAJUS 3 [hp_X]/59 mL; ARTEMISIA VULGARIS POLLEN 6 [hp_X]/59 mL; PLANTAGO LANCEOLATA POLLEN 6 [hp_X]/59 mL; SOLIDAGO VIRGAUREA POLLEN 6 [hp_X]/59 mL; GOLDENSEAL 5 [hp_X]/59 mL; HISTAMINE DIHYDROCHLORIDE 60 [hp_X]/59 mL; SORGHUM HALEPENSE POLLEN 6 [hp_X]/59 mL; POA PRATENSIS POLLEN 6 [hp_X]/59 mL; ACER PSEUDOPLATANUS POLLEN 6 [hp_X]/59 mL; NASTURTIUM OFFICINALE 3 [hp_X]/59 mL; QUERCUS SPP. WHOLE 6 [hp_X]/59 mL; DACTYLIS GLOMERATA POLLEN 6 [hp_X]/59 mL; AMARANTHUS RETROFLEXUS POLLEN 6 [hp_X]/59 mL; PINUS MASSONIANA POLLEN 6 [hp_X]/59 mL; AMBROSIA ARTEMISIIFOLIA 6 [hp_X]/59 mL; JUNIPERUS VIRGINIANA POLLEN 6 [hp_X]/59 mL; MORUS RUBRA POLLEN 6 [hp_X]/59 mL; SCROPHULARIA NODOSA 3 [hp_X]/59 mL; RUMEX ACETOSELLA POLLEN 6 [hp_X]/59 mL; SOLIDAGO VIRGAUREA FLOWERING TOP 3 [hp_X]/59 mL; ANTHOXANTHUM ODORATUM POLLEN 6 [hp_X]/59 mL; TARAXACUM OFFICINALE POLLEN 3 [hp_X]/59 mL; PHLEUM PRATENSE POLLEN 6 [hp_X]/59 mL; POPULUS ALBA POLLEN 6 [hp_X]/59 mL
INACTIVE INGREDIENTS: ALCOHOL; GLYCERIN; WATER

OHM Allergy Grass, Weed, Tree Mix

ACTIVE INGREDIENT

ACTIVE INGREDIENTS: Equal amounts of: Bermuda 6X, Birch Mix 6X, Brome 6X, Carduus Marianus 3X, Chelidonium Majus 3X, Common Mugwort 6X, English Plantain 6X, Goldenrod 6X, Hydrastis Canadensis 5X, Histam. 60X, 400X, Johnson 6X, Kentucky 6X, Maple Mix 6X, Nasturtium Aqua 3X, Oak Mix #2 6X, Orchard 6X, Pigweed Mix 6X, Pine Mix 6X, Ragweed Mix #2 6X, Red Cedar 6X, Red Mulb. 6X, Scrophularia Nod. 3X, Sheep Sorrel 6X, Soildago Virg. 3X, Sweet Vernal 6X, Taraxacum Offi. 3X, Timothy 6X, White Poplar 6X.

INDICATIONS AND USAGE

USES: Temporarily relieves sneezing, runny nose, itchy eyes and congestion associated with exposure to grasses, weeds and trees.

**This statement has not been evaluated by the FDA. It is based on documented Homeopathic Materia Medica.

WARNINGS

WARNINGS: IF PREGNANT OR BREAST-FEEDING, ask a health professional before use. If symptoms worsen or persist for more than a week, discontinue use and contact a doctor.

- KEEP OUT OF REACH OF CHILDREN.

DOSAGE AND ADMINISTRATION

DIRECTIONS: Shake 10 times before use. Adults & children above 12 years of age: spray 3-4 times under the tongue every 15 minutes, extend intervals as symptoms improve, or as directed by a health care professional. Children under 12 years: use half the adult dose.

Do not use if cap seal is broken.

INACTIVE INGREDIENT

INACTIVE INGREDIENTS: Ethyl Alcohol 15% (Non-GMO, Kosher Certified, Corn, Gluten, Allergen Free), Glycerin, Purified Water.

QUESTIONS

Mfg. By: OHM PHARMA, INC Mineral Wells, TX

www.ohmpharma.com

PACKAGE LABEL

HOMEOPATHIC MEDICINE

NDC: 66096-671-05

ALLERGY Grass/Weed/Tree Mix

Natural - Safe - Effective

No Side Effects

2 fl oz (59 mL) / 15% Alcohol

PURPOSE

Allergy Mix